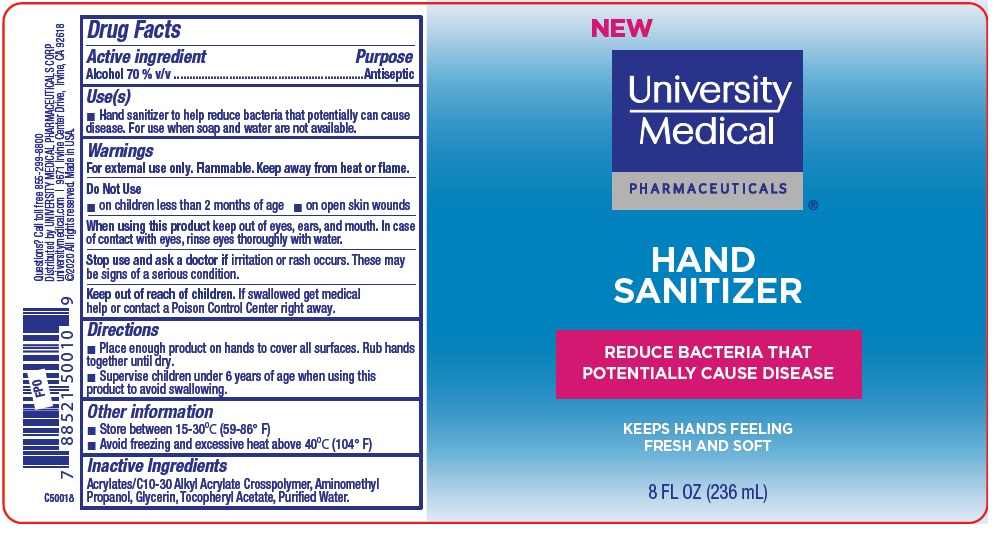 DRUG LABEL: University Medical PHARMACEUTICALS HAND SANITIZER
NDC: 50544-888 | Form: LIQUID
Manufacturer: University Medical Pharmaceuticals Corp.
Category: otc | Type: HUMAN OTC DRUG LABEL
Date: 20200509

ACTIVE INGREDIENTS: ALCOHOL 70 mL/100 mL
INACTIVE INGREDIENTS: CARBOMER INTERPOLYMER TYPE A (ALLYL SUCROSE CROSSLINKED); AMINOMETHYLPROPANOL; GLYCERIN; .ALPHA.-TOCOPHEROL ACETATE; WATER

University Medical PHARMACEUTICALS ® HAND SANITIZER

Active ingredient

Alcohol 70% v/v

Purpose

Antiseptic

Use(s)

■ Hand sanitizer to help reduce bacteria that potentially can cause disease. For use when soap and water are not available.

Warnings

For external use only. Flammable. Keep away from heat or flame.

Do Not Use

■ on children less than 2 months of age ■ on open skin wounds

When using this product keep out of eyes, ears, and mouth. In case of contact with eyes, rinse eyes thoroughly with water.

Stop use and ask a doctorif irritation or rash occurs. These may be signs of a serious condition.

Keep out of reach of children. If swallowed, get medical help or contact a Poison Control Center right away.

Directions

■ Place enough product on hands to cover all surfaces. Rub hands together until dry.

■ Supervise children under 6 years of age when using this product to avoid swallowing.

Other information

■ Store between 15-30°C (59-86°F)

■ Avoid freezing and excessive heat above 40°C (104°F)

Inactive Ingredients

Acrylates/C10-30 Alkyl Acrylate Crosspolymer, Aminomethyl Propanol, Glycerin, Tocopheryl Acetate, Purified Water.

NEW

REDUCE BACTERIA THAT POTENTIALLY CAUSE DISEASE

KEEPS HANDS FEELING FRESH AND SOFT

Questions? Call toll free 855-299-8800

Distributed by UNIVERSITY MEDICAL PHARMACEUTICALS CORP
universitymedical.com | 9671 Irvine Center Drive, Irvine, CA 92618

©2020 All rights reserved. Made in USA.